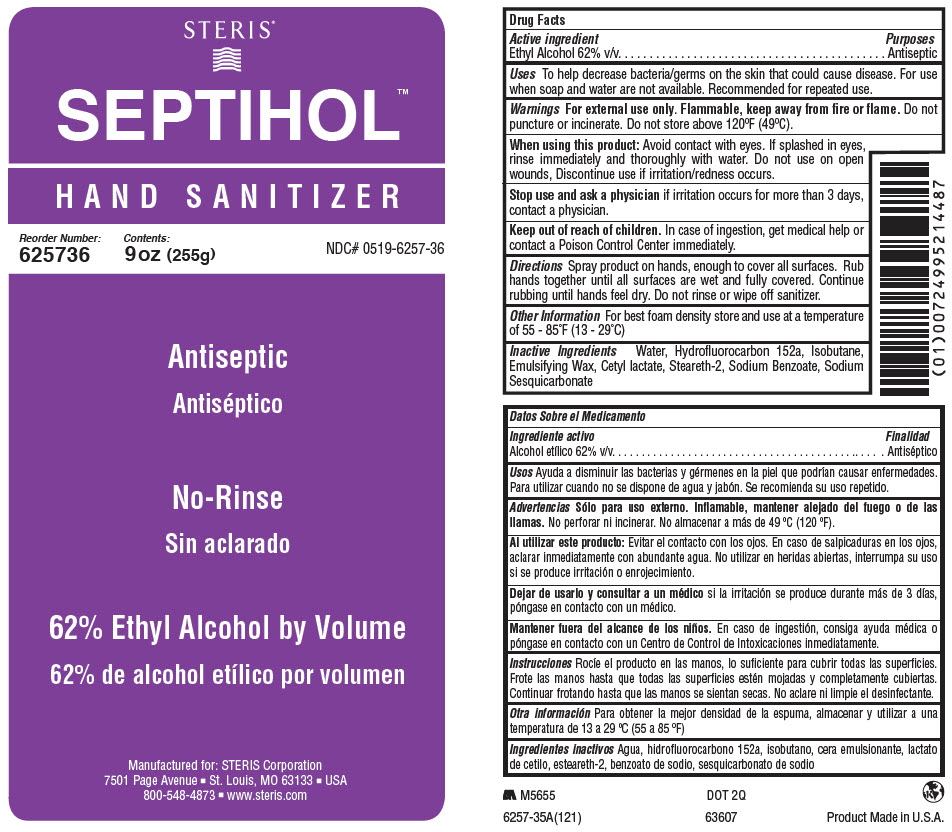 DRUG LABEL: Septihol Hand Sanitizer
NDC: 0519-6257 | Form: AEROSOL, FOAM
Manufacturer: STERIS Corporation
Category: otc | Type: HUMAN OTC DRUG LABEL
Date: 20231206

ACTIVE INGREDIENTS: Alcohol 62 mL/100 mL
INACTIVE INGREDIENTS: water; 1,1-Difluoroethane; Isobutane; Cetyl lactate; Steareth-2; Sodium Benzoate; SODIUM SESQUICARBONATE

Septihol™ Hand Sanitizer

Drug Facts

Active ingredient

Ethyl Alcohol 62% v/v

Purposes

Antiseptic

Uses

To help decrease bacteria/germs on the skin that could cause disease. For use when soap and water are not available. Recommended for repeated use.

Warnings

For external use only. Flammable, keep away from fire or flame. Do not puncture or incinerate. Do not store above 120ºF (49ºC).

When using this product

Avoid contact with eyes. If splashed in eyes, rinse immediately and thoroughly with water. Do not use on open wounds, Discontinue use if irritation/redness occurs.

Stop use and ask a physician if irritation occurs for more than 3 days, contact a physician.

Keep out of reach of children. In case of ingestion, get medical help or contact a Poison Control Center immediately.

Directions

Spray product on hands, enough to cover all surfaces. Rub hands together until all surfaces are wet and fully covered. Continue rubbing until hands feel dry. Do not rinse or wipe off sanitizer.

Other Information

For best foam density store and use at a temperature of 55 - 85˚F (13 - 29˚C)

Inactive Ingredients

Water, Hydrofluorocarbon 152a, Isobutane, Emulsifying Wax, Cetyl lactate, Steareth-2, Sodium Benzoate, Sodium Sesquicarbonate

PRINCIPAL DISPLAY PANEL - 255 g Bottle Label

STERIS®

SEPTIHOL™

HAND SANITIZER

Reorder Number:
625736

Contents:
9 oz (255g)

NDC# 0519-6257-36

Antiseptic

No-Rinse

62% Ethyl Alcohol by Volume

Manufactured for: STERIS Corporation
7501 Page Avenue ■ St. Louis, MO 63133 ■ USA
800-548-4873 ■ www.steris.com